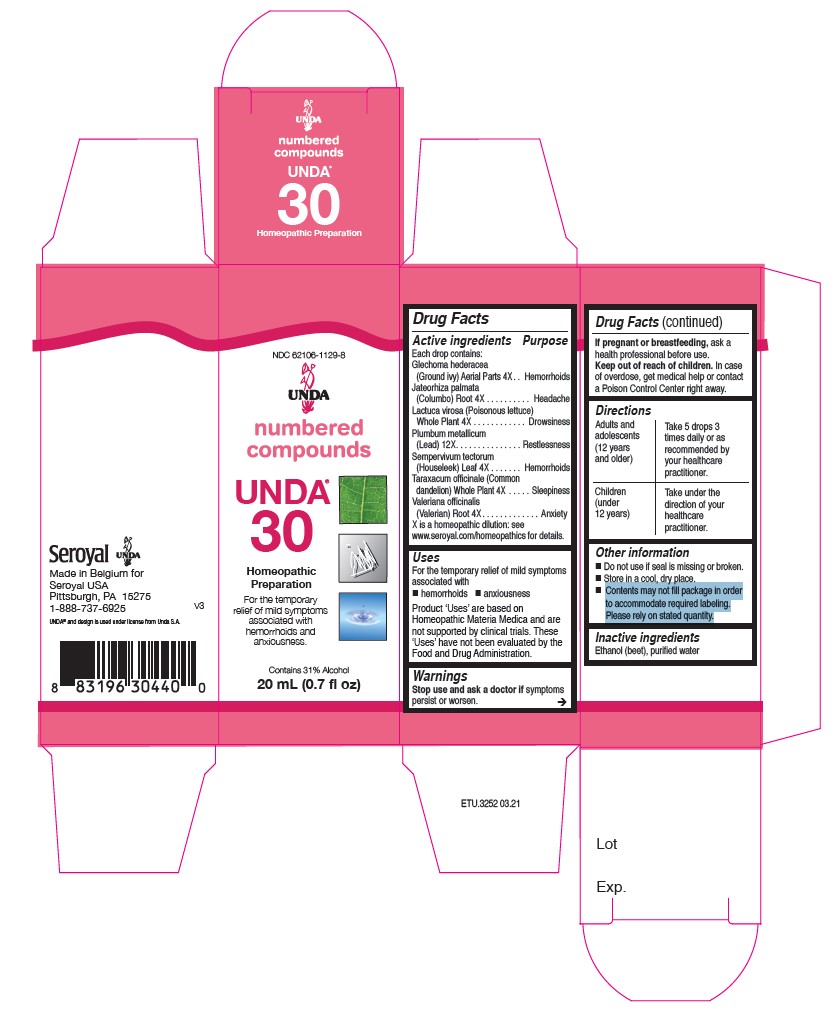 DRUG LABEL: Unda 30
NDC: 62106-1129 | Form: LIQUID
Manufacturer: Seroyal USA
Category: homeopathic | Type: HUMAN OTC DRUG LABEL
Date: 20210715

ACTIVE INGREDIENTS: LACTUCA VIROSA 4 [hp_X]/20 mL; LEAD 12 [hp_X]/20 mL; SEMPERVIVUM TECTORUM LEAF 4 [hp_X]/20 mL; VALERIAN 4 [hp_X]/20 mL; GLECHOMA HEDERACEA 4 [hp_X]/20 mL; JATEORHIZA CALUMBA ROOT 4 [hp_X]/20 mL; TARAXACUM OFFICINALE WHOLE 4 [hp_X]/20 mL
INACTIVE INGREDIENTS: ALCOHOL; WATER

Unda 30

Active ingredients

Each drop contains:
Glechoma hederacea (Ground ivy) Aerial Parts 4X
Jateorhiza palmata (Columbo) Root 4X
Lactuca virosa (Poisonous lettuce) Whole Plant 4X
Plumbum metallicum (Lead) 12X
Sempervivum tectorum (Houseleek) Leaf 4X
Taraxacum officinale (Common dandelion) Whole Plant 4X
Valeriana officinalis (Valerian) Root 4X

Uses

For the temporary relief of mild symptoms associated with hemorrhoids and anxiousness

Warnings
Stop use and ask a doctor if symptoms persist or worsen.

If pregnant or breastfeeding, ask a health professional before use.
Keep out of reach of children.

In case of overdose, get medical help or contact a Poison Control Center right away.

Stop use and ask a doctor if symptoms persist or worsen.

PREGNANCY OR BREAST FEEDING

If pregnant or breastfeeding, ask a health professional before use.

Keep out of reach of children.

OVERDOSAGE

In case of overdose, get medical help or contact a Poison Control Center right away.

Inactive ingredients
Ethanol (beet), purified water

Other information
Do not use if seal is missing or broken.
Store in a cool, dry place.

Contents may not fill package in order
to accommodate required labeling.
Please rely on stated quantity.

Directions
Adults and adolescents (12 years and older)

Take 5 drops three times daily or as recommended by your healthcare practitioner.

Children (under 12 years)

Take under the direction of your healthcare practitioner.

Uses

For the temporary relief of mild symptoms associated with hemorrhoids and anxiousness.

Directions
Adults and adolescents (12 years and older)

Take 5 drops three times daily or as recommended by your healthcare practitioner.

Children (under 12 years)

Take under the direction of your healthcare practitioner.

PACKAGE LABEL

NDC 62106-1129-8

UNDA

numbered compounds

UNDA 30

Homeopathic Preparation

For the temporary relief of mild symptoms associated with hemorrhoids and anxiousness.

Contains 31% Alcohol
0.7 fl oz (20 ml)